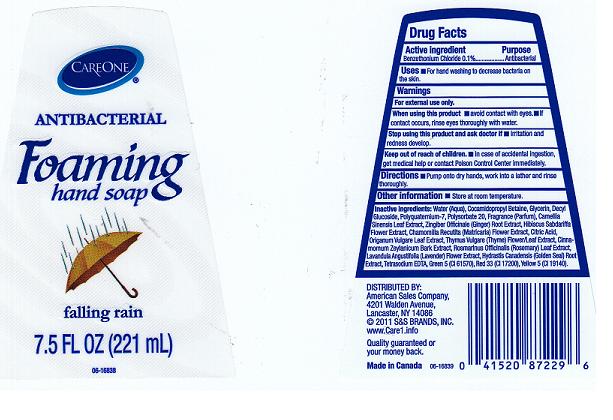 DRUG LABEL: CAREONE ANTIMICROBIAL FOAMING HAND SP FALLING RAIN
NDC: 41520-241 | Form: LIQUID
Manufacturer: AMERICAN SALES COMPANY
Category: otc | Type: HUMAN OTC DRUG LABEL
Date: 20110525

ACTIVE INGREDIENTS: BENZETHONIUM CHLORIDE 0.1 mL/100 mL
INACTIVE INGREDIENTS: WATER; COCAMIDOPROPYL BETAINE; GLYCERIN; DECYL GLUCOSIDE; POLYQUATERNIUM-7 (70/30 ACRYLAMIDE/DADMAC; 1600 KD); POLYSORBATE 20; GREEN TEA LEAF; GINGER; HIBISCUS SABDARIFFA FLOWER; CHAMOMILE; CITRIC ACID MONOHYDRATE; OREGANO; THYME; CINNAMON BARK OIL; ROSEMARY; LAVANDULA ANGUSTIFOLIA FLOWER; GOLDENSEAL; EDETATE SODIUM; D&C GREEN NO. 5; D&C RED NO. 33; FD&C YELLOW NO. 5

DRUG FACTS

ACTIVE INGREDIENT

BENZETHONIUM CHLORIDE 0.1 PERCENT

PURPOSE

ANTIBACTERIAL

USES

FOR HAND WASHING TO DECREASE BACTERIA ON THE SKIN.

WARNINGS

FOR EXTERNAL USE ONLY.

KEEP OUT OF REACH OF CHILDREN

IN CASE OF ACCIDENTAL INGESTION, GET MEDICAL HELP OR CONTACT POISON CONTROL CENTER IMMEDIATELY.

WHEN USING THIS PRODUCT

AVOID CONTACT WITH EYES. IF CONTACT OCCURS, RINSE EYES THOROUGHLY WITH WATER.

STOP USING THIS PRODUCT AND ASK A DOCTOR

IF IRRITATION OR RASH DEVELOPS AND LASTS.

DIRECTIONS

PUMP ONTO DRY HANDS, WORK INTO A LATHER AND RINSE THOROUGHLY.

OTHER INFORMATION

STORE AT ROOM TEMPERATURE.

INACTIVE INGREDIENTS

WATER, COCAMIDOPROPYL BETAINE, GLYCERIN, DECYL GLUCOSIDE, POLYQUATERNIUM-7, POLYSORBATE 20, FRAGRANCE, CAMELLIA SINENSIS LEAF EXTRACT, ZINGIBER OFFICINALE (GINGER) ROOT EXTRACT, HIBISCUS SABDARIFFA FLOWER EXTRACT, CHAMOMILLA RECUTITA (MATRICARIA) FLOWER EXTRACT, CITRIC ACID, ORIGANUM VULGARE LEAF EXTRACT, THYMUS VULGARE (THYME) FLOWER/ LEAF EXTRACT, CINNAMOMUM ZEYLANICUM BARK EXTRACT, ROSMARINUS OFFICINALIS (ROSEMARY) LEAF EXTRACT, LAVANDULA ANGUSTIFOLIA (LAVENDER) FLOWER EXTRACT, HYDRASTIS CANADENSIS (GOLDEN SEAL) ROOT EXTRACT, TETRASODIUM EDTA, GREEN 5 (CI 61570), RED 33 (CI 17200), YELLOW 5 (CI 19140).